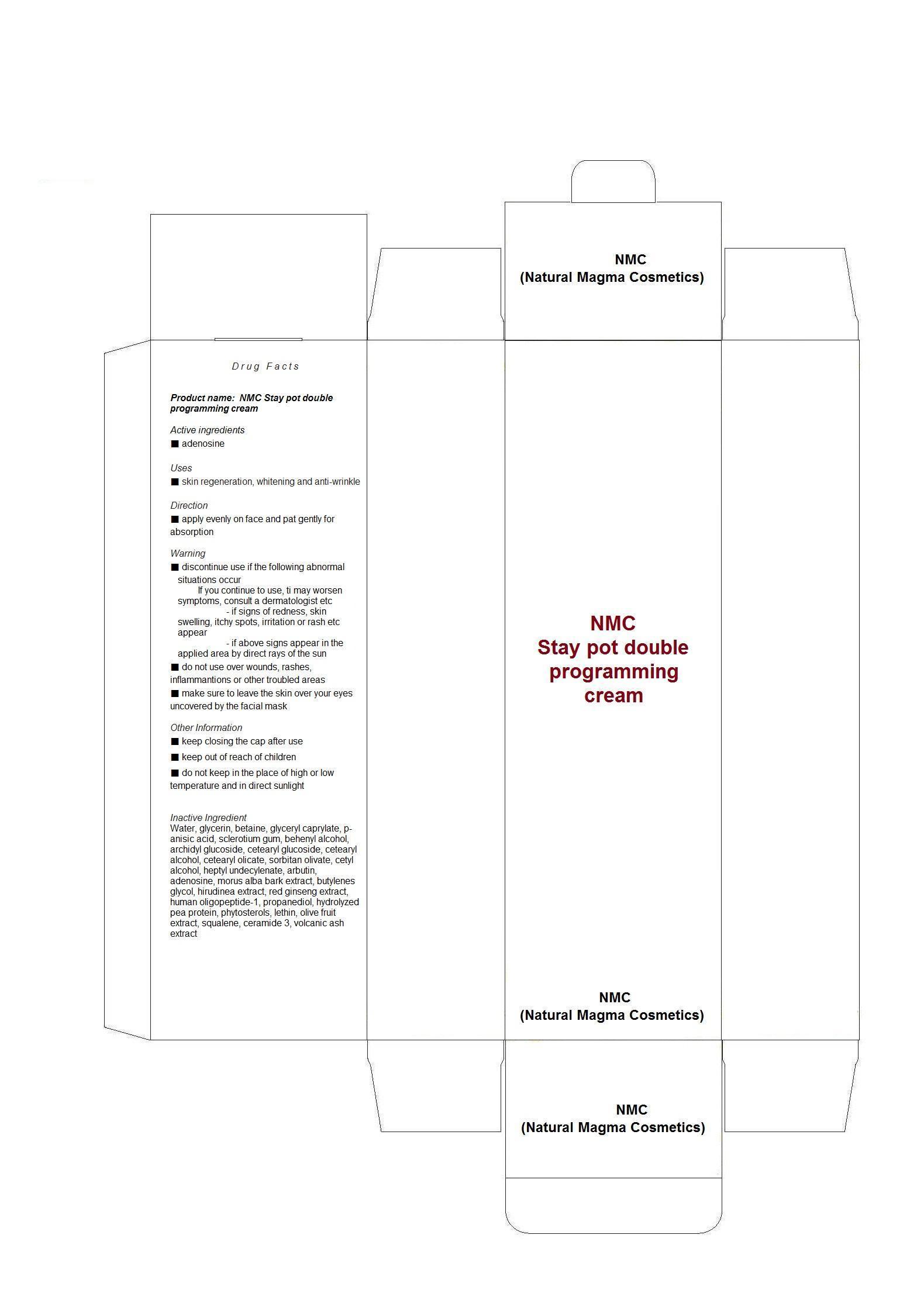 DRUG LABEL: NMC Magic Serum
NDC: 59220-3001 | Form: LIQUID
Manufacturer: NMC (Natural Magma Cosmetics)
Category: otc | Type: HUMAN OTC DRUG LABEL
Date: 20130711

ACTIVE INGREDIENTS: ADENOSINE 0.04 mg/100 mL
INACTIVE INGREDIENTS: WATER; GLYCERIN; BETAINE; GLYCERYL CAPRYLATE; P-ANISIC ACID; DOCOSANOL; CETEARYL GLUCOSIDE; CETOSTEARYL ALCOHOL; SORBITAN OLIVATE; SQUALENE; PROPANEDIOL

Drug Facts

ACTIVE INGREDIENT

adenosine

INACTIVE INGREDIENT

Water, glycerin, betaine, glyceryl caprylate, p-anisic acid, sclerotium gum, behenyl alcohol, archidyl glucoside, cetearyl glucoside, cetearyl alcohol, cetearyl olicate, sorbitan olivate, cetyl alcohol, heptyl undecylenate, arbutin, adenosine, morus alba bark extract, butylenes glycol, hirudinea extract, red ginseng extract, human oligopeptide-1, propanediol, hydrolyzed pea protein, phytosterols, lethin, olive fruit extract, squalene, ceramide 3, volcanic ash extract

PURPOSE

skin regeneration, whitening and anti-wrinkle

keep out or reach of the children

INDICATIONS AND USAGE

apply evenly on face and pat gently for absorption

WARNINGS

■ discontinue use if the following abnormal situations occur
If you continue to use, ti may worsen symptoms, consult a dermatologist etc
- if signs of redness, skin swelling, itchy spots, irritation or rash etc appear
- if above signs appear in the applied area by direct rays of the sun
■ do not use over wounds, rashes, inflammantions or other troubled areas
■ make sure to leave the skin over your eyes uncovered by the facial mask
Other Information
■ keep closing the cap after use
■ keep out of reach of children
■ do not keep in the place of high or low temperature and in direct sunlight

DOSAGE AND ADMINISTRATION

for topical use only